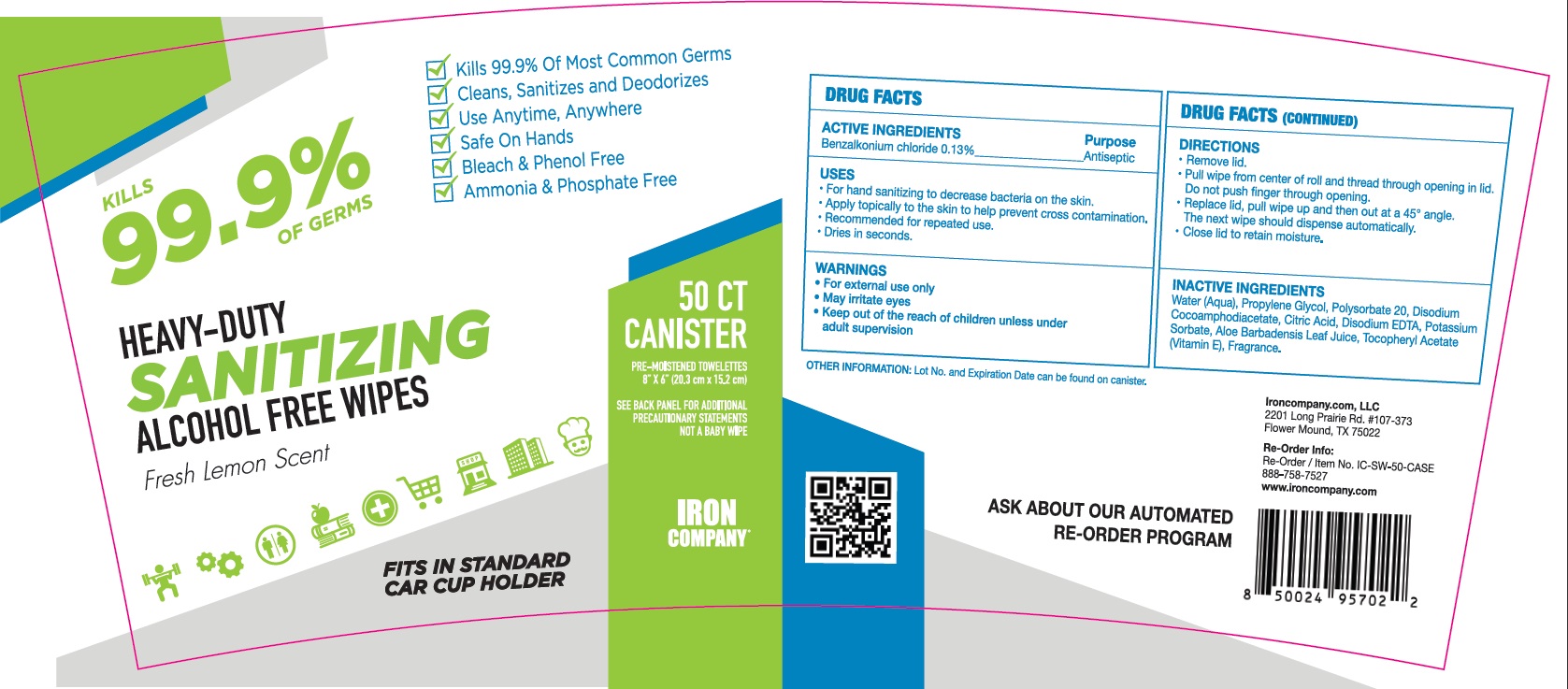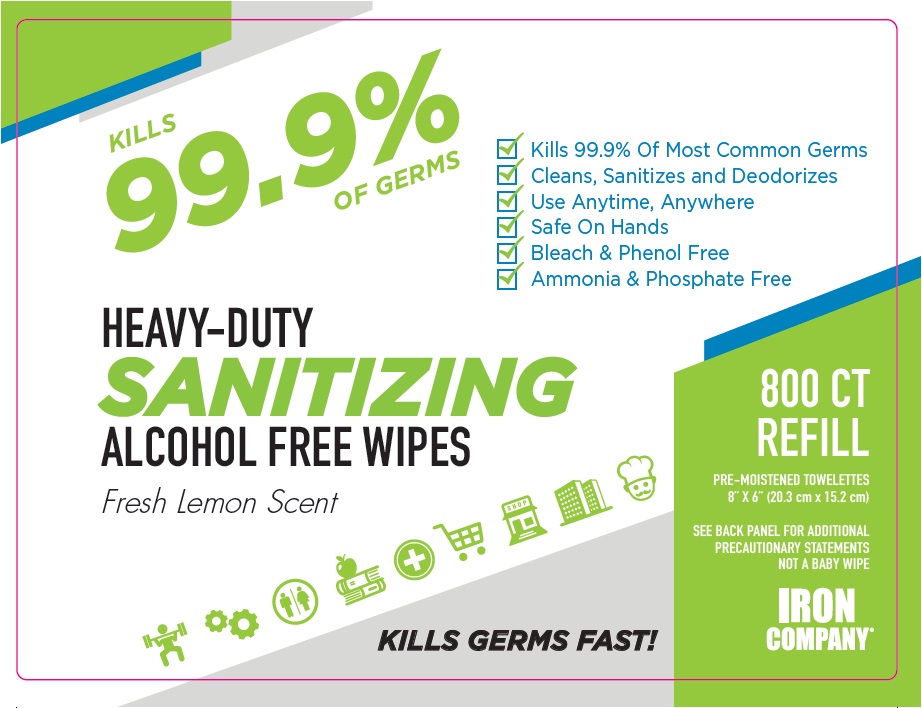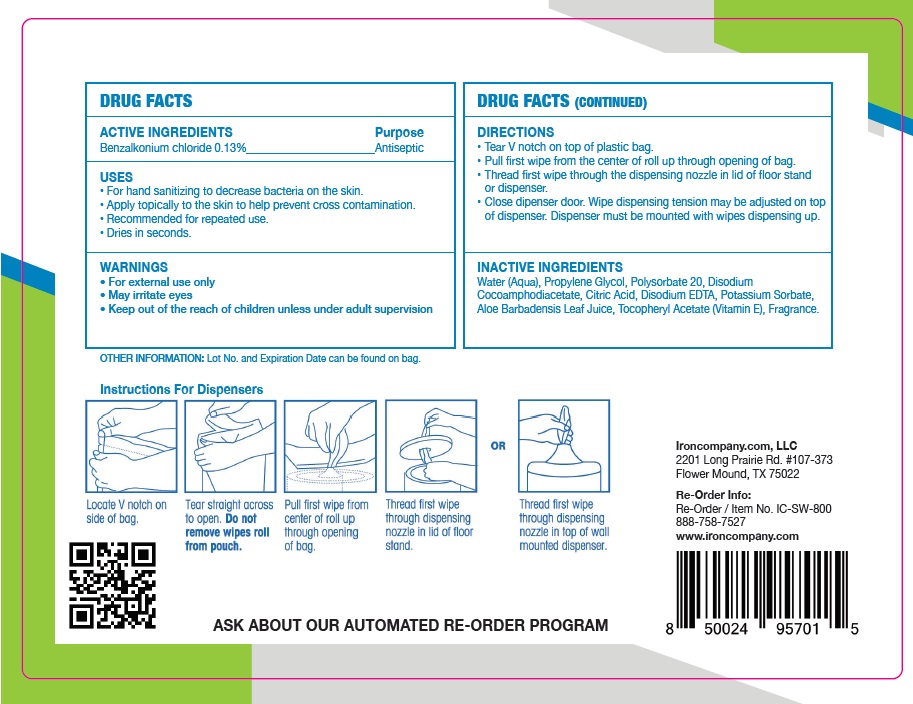 DRUG LABEL: SANITIZING WIPES
NDC: 75127-101 | Form: CLOTH
Manufacturer: Jurong Dongfa General Merchandise Co Ltd
Category: otc | Type: HUMAN OTC DRUG LABEL
Date: 20210202

ACTIVE INGREDIENTS: BENZALKONIUM CHLORIDE 0.13 g/100 g
INACTIVE INGREDIENTS: WATER; CITRIC ACID MONOHYDRATE; EDETATE SODIUM; DISODIUM COCOAMPHODIACETATE; PROPYLENE GLYCOL; POLYSORBATE 20; ALOE VERA LEAF; POTASSIUM SORBATE; ALPHA-TOCOPHEROL ACETATE

75127-101 SANITIZING ALCOHOL FREE WIPES 0.13% Benzalkonium chloride

Active Ingredient

Benzalkonium Chloride 0.13%

Purpose

Antiseptic

USE

●For hand sanitizing to decrease bacteria on the skin.
●Apply topically to the skin to help prevent cross contamination.
●Recommended for repeated use.
●Dries in seconds.

Warning

For external use only
May irritate eyes

●Keep out of reach of children unless under adult supervision.

Directions

.Tear V notch on top of plastic bag.
. Pull first wipe from the center of roll up through opening of bag. Thread first wipe through the dispensing nozzle in lid of floor stand or dispenser.
- Close dipenser door. Wipe dispensing tension may be adjusted on top of dispenser. Dispenser must be mounted with wipes dispensing up.

Inactive ingredients

Water (Aqua),Propylene Glycol,Polysorbate 20,Disodium
Cocoamphodiacetate, Citric Acid, Disodium EDTA, Potassium Sorbate,Aloe Barbadensis Leaf Juice,TocopheryI Acetate (Vitamin E), Fragrance.